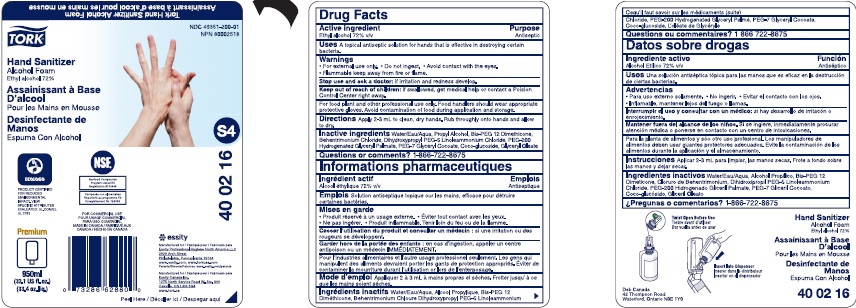 DRUG LABEL: Tork Hand Sanitizer Alcohol Foam
NDC: 49351-200 | Form: LIQUID
Manufacturer: ESSITY NORTH AMERICA INC.
Category: otc | Type: HUMAN OTC DRUG LABEL
Date: 20190608

ACTIVE INGREDIENTS: ALCOHOL 0.72 mL/1 mL
INACTIVE INGREDIENTS: WATER; PROPYL ALCOHOL; DIMETHICONE; BEHENTRIMONIUM CHLORIDE; DIHYDROXYPROPYL PEG-5 LINOLEAMMONIUM CHLORIDE; PEG-200 DILAURATE; GLYCERYL COCOATE; COCO GLUCOSIDE; GLYCERYL MONOOLEATE

PACKAGE LABEL

Tork Hand Sanitizer Alcohol Foam
Assainissant a base d'alcool pour les mains en mouse
TORK
Hand Sanitizer
Alcohol Foam
Ethyl alcohol 72%
Assainissant a Base
D'alcool
Pour les Mains en Mousse
Desinfectante de Manos
Espuma Con Alcohol
S4
40 02 16
Essity
Manufactured for / Fabrique pour / Fabricado para
Essity Professional Hygiene North America LLC
2929 Arch Street
Philadelphia, PA 19104
www.essity.com, www.torkusa.com
Patents/Brevets/Patentes: www.essity.com/patents
Manufactured for / Fabrique pour / Fabricado para
Essity Canada Inc.
1275 North Service Road W. Ste. 800
Oakville, ON L6M 3G4
www.tork.ca
Premium
950 mL
(32.1 US fl. oz.)
(33.4 oz. liq.)
NSF
FOR COMMERCIAL USE
POUR USAGE COMMERCIAL
PARA USO COMMERCIAL
MADE IN CANADA / FABRIQUE AUX
CANADA / HECHO EN CANADA
Peel here / Decoller ici / Despegar aqui